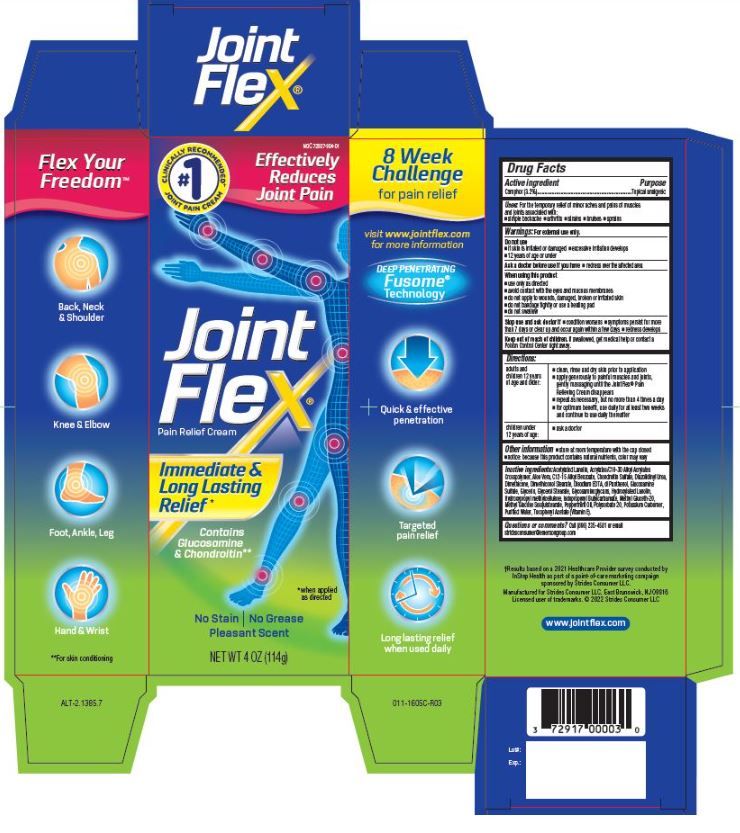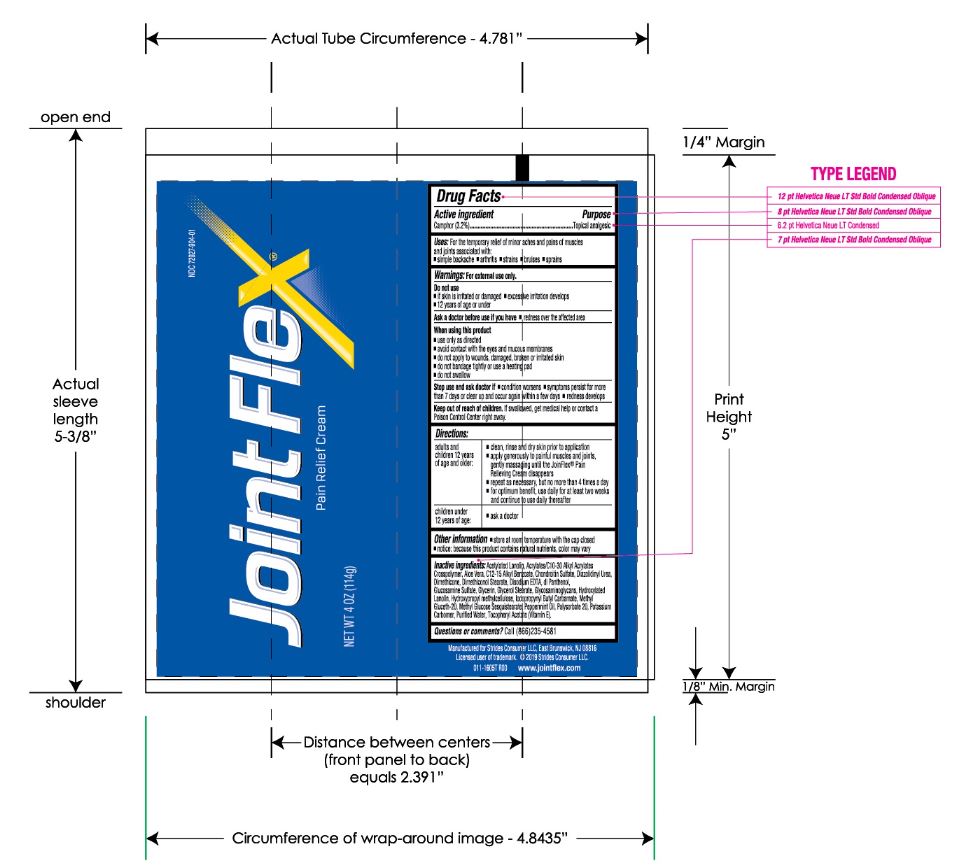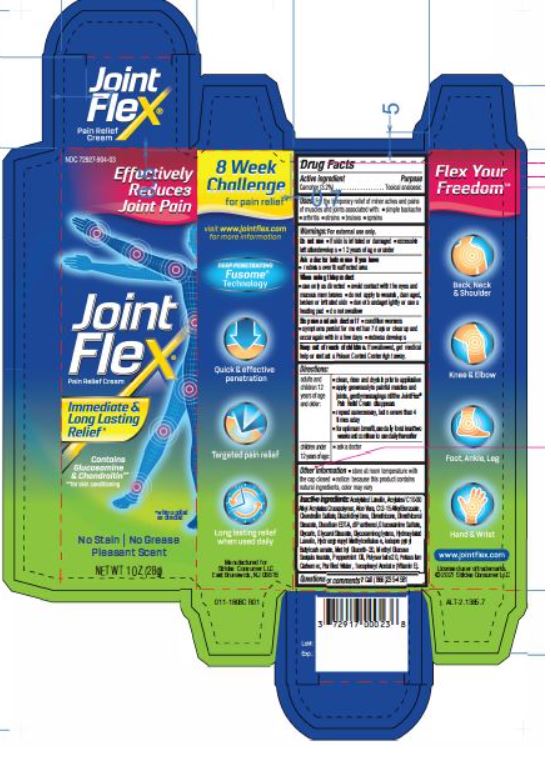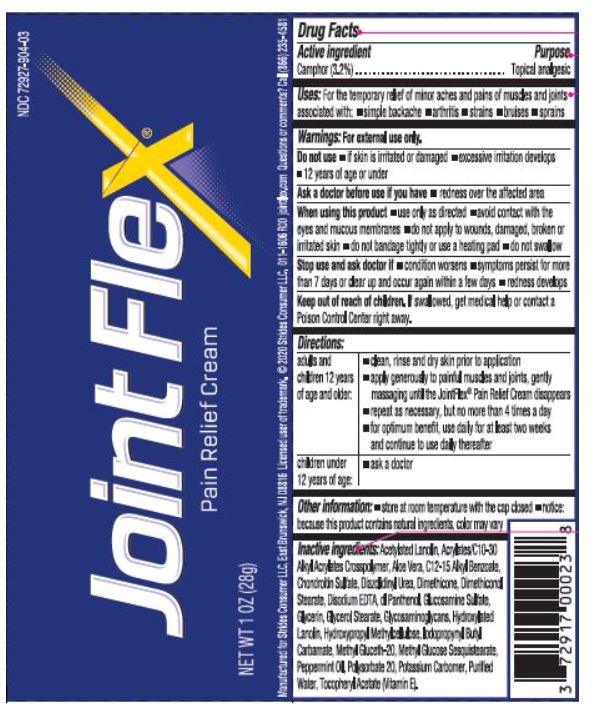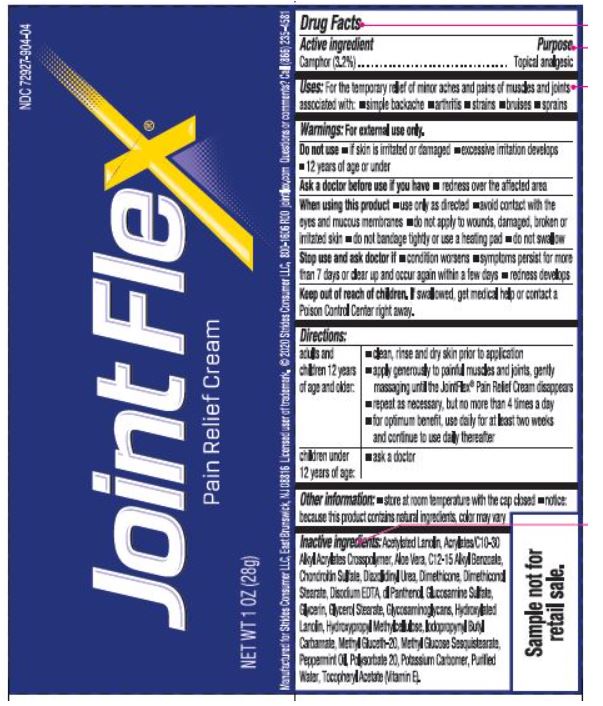 DRUG LABEL: Jointflex
NDC: 72927-904 | Form: CREAM
Manufacturer: Strides Consumer LLC
Category: otc | Type: HUMAN OTC DRUG LABEL
Date: 20250409

ACTIVE INGREDIENTS: CAMPHOR (SYNTHETIC) 3.2 g/100 g
INACTIVE INGREDIENTS: ALPHA-TOCOPHEROL ACETATE; ACETYLATED LANOLIN; ALKYL (C12-15) BENZOATE; ALOE VERA LEAF; CARBOMER 1342; CARBOMER INTERPOLYMER TYPE A (55000 CPS); CHONDROITIN SULFATE (SHARK); DIAZOLIDINYL UREA; DIMETHICONE; EDETATE DISODIUM; GLUCOSAMINE SULFATE POTASSIUM CHLORIDE; GLYCERIN; GLYCERYL MONOSTEARATE; HYDROXYLATED LANOLIN; HYPROMELLOSES; IODOPROPYNYL BUTYLCARBAMATE; METHYL GLUCETH-20; METHYL GLUCOSE SESQUISTEARATE; PANTHENOL; PEPPERMINT OIL; POLYOXYL 40 STEARATE; POLYSORBATE 20; POTASSIUM HYDROXIDE; SHARK CARTILAGE; WATER

JointFlex®
Pain Relief Cream
Drug Facts

Actice Ingredient

Camphor (3.2%)

Purpose

Topical analgesic

Uses:

For the temporary relief of minor aches and pains of muscles and joints associated with:

- simple backache
- arthritis
- strains
- bruises
- sprains

Warnings:

For external use only.

Do not use

- if skin is irritated or damaged
- excessive irritation develops
- 12 years of age or under

Ask a doctor before use if you have

- redness over the affected area

When using this product

- use only as directed
- avoid contact with the eyes and mucous membranes
- do not apply to wounds, damaged, broken or irritated skin
- do not bandage tightly or use a heating pad
- do not swallow

Stop use and ask doctor if

- condition worsens
- symptoms persist for more than 7 days or clear up and occur again within a few days
- redness develops

Keep out of reach of children.

If swallowed, get medical help or contact a Poison Control Center right away.

Directions:

adults and children 12 years of age and older: | - clean, rinse and dry skin prior to application; - apply generously to painful muscles and joints, gently massaging until the JointFlex® Pain Relieving Cream disappears; - repeat as necessary, but no more than 4 times a day; - for optimum benefit, use daily for at least two weeks and continue to use daily thereafter
children under 12 years of age: | - ask a doctor

Other information

- store at room temperature with the cap closed
- notice: because this product contains natural nutrients, color may vary

Inactive ingredients:

Acetylated Lanolin, Acrylates/C10-30 Alkyl Acrylate Crosspolymer, Aloe Vera, C12-15 Alkyl Benzoate, Chondroitin Sulfate, Diazolidinyl Urea, Dimethicone, Dimethiconol Stearate, Disodium EDTA, dl Panthenol, Glucosamine Sulfate, Glycerin, Glycerol Stearate, Glycosaminoglycans, Hydroxylated Lanolin, Hydroxypropyl methycellulose, Iodopropynyl Butylcarbamate, Methyl Gluceth-20, Methyl Glucose Sesquistearate, Peppermint Oil, Polysorbate 20, Potassium Carbomer, Purified Water, Tocopheryl Acetate (Vitamin E).

Questions and comments?

Call (866) 235-4581 or or email stridesconsumer@emersongroup.com

Manufactured for

Strides Consumer LLC,

East Brunswick, NJ 08816

†Results based on a 2021 Healthcare Provider survey conducted by InStep Health as part of a point-of-care marketing campaign sponsored by Strides Consumer LLC.

Manufactured for Strides Consumer LLC, East Brunswick, NJ 08816

Licensed user of trademarks. © 2022 Strides Consumer LLC

www.jointflex.com

PACKAGE LABEL.PRINCIPAL DISPLAY PANEL

8 Week Challenge for pain relief

Effectively Reduces Joint Pain

#1 CLINICALLY RECOMMENDED† JOINT PAIN CREAM

JointFlex®- Pain Relief Cream

Immediate & Long Lasting Relief*

Contains Glucosamine & Chondroitin**

No stain/ No Grease/ Pleasant Scent

DEEP PENETRATINGFusome® Technology

Quick & effective penetration

Targeted pain relief

Long lasting relief when used daily

Flex Your Freedom™

Relieves Back, Neck, Shoulder, Knees, Elbow, Foot, Ankle, Leg Hand and Wrist pain

NET WT 4 OZ (114g)

NDC 72927-904-01

Visit www.jointflex.com for more information

* when applied as directed

** For skin conditioning

011-1605C-R03

Carton label

Tube label

8 Week Challenge for pain relief

Effectively Reduces Joint Pain

JointFlex®- Pain Relief Cream

Immediate & Long Lasting Relief*

Contains Glucosamine & Chondroitin**

No stain/ No Grease/ Pleasant Scent

DEEP PENETRATINGFusome® Technology

Quick & effective penetration

Targeted pain relief

Long lasting relief when used daily

Flex Your Freedom™

Relieves Back, Neck, Shoulder, Knees, Elbow, Foot, Ankle, Leg Hand and Wrist pain

NET WT 1 OZ (28g)

NDC 72927-904-03

Visit www.jointflex.com for more information

* when applied as directed

** For skin conditioning

011-1606C-R01

Carton Label

Tube Label

8 Week Challenge for pain relief

Effectively Reduces Joint Pain

JointFlex®- Pain Relief Cream

Immediate & Long Lasting Relief*

Contains Glucosamine & Chondroitin**

No stain/ No Grease/ Pleasant Scent

DEEP PENETRATINGFusome® Technology

Quick & effective penetration

Targeted pain relief

Long lasting relief when used daily

Flex Your Freedom™

Relieves Back, Neck, Shoulder, Knees, Elbow, Foot, Ankle, Leg Hand and Wrist pain

NET WT 1 OZ (28g)

NDC 72927-904-04

Visit www.jointflex.com for more information

* when applied as directed

** For skin conditioning

Sample not for retail sale.